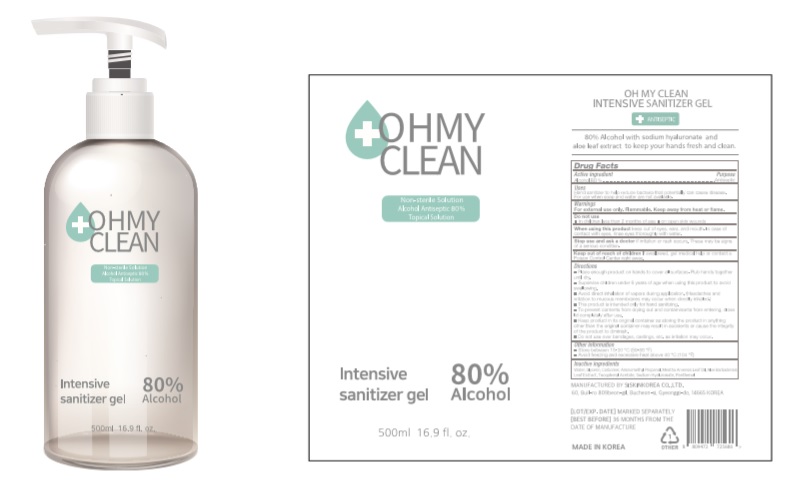 DRUG LABEL: OHMYCLEAN Intensive sanitizer gel
NDC: 74514-0580 | Form: GEL
Manufacturer: SISKINKOREA CO.,LTD.
Category: otc | Type: HUMAN OTC DRUG LABEL
Date: 20200420

ACTIVE INGREDIENTS: ALCOHOL 400 mL/500 mL
INACTIVE INGREDIENTS: PANTHENOL; MENTHA ARVENSIS LEAF OIL; GLYCERIN; .ALPHA.-TOCOPHEROL ACETATE; ALOE VERA LEAF; WATER; AMINOMETHYL PROPANEDIOL; CARBOMER HOMOPOLYMER, UNSPECIFIED TYPE; HYALURONATE SODIUM

500ml_80%_gel_OHMYCLEAN Intensive sanitizer gel[74514-0580-1]